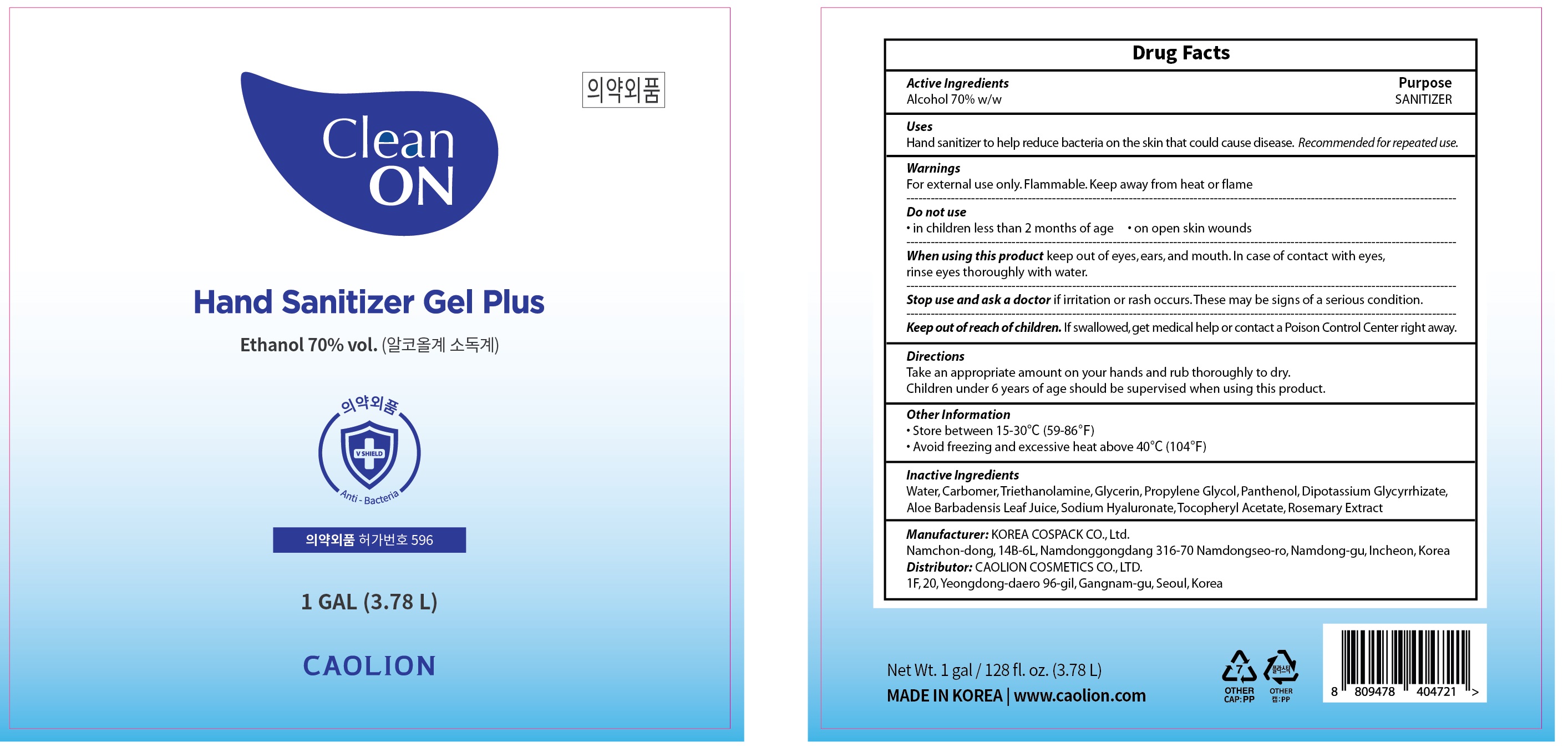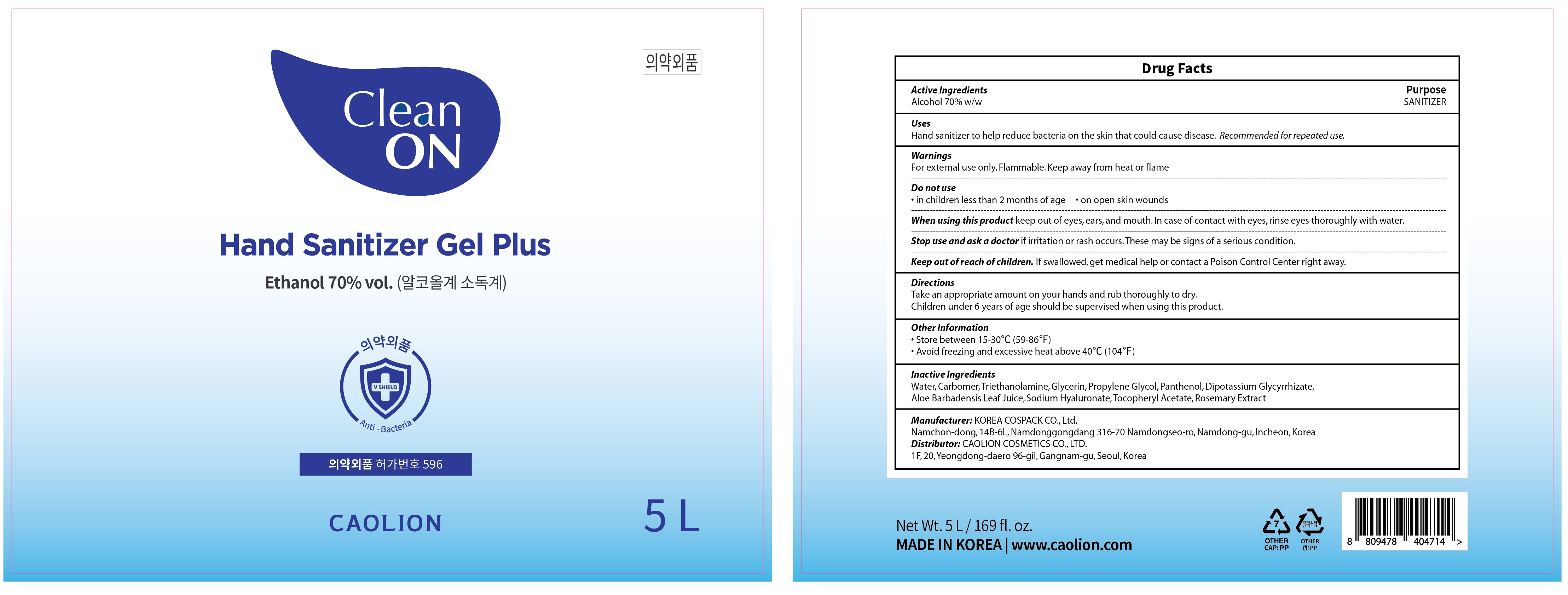 DRUG LABEL: CLEAN ON HAND SANITIZER PLUS
NDC: 74522-030 | Form: GEL
Manufacturer: Caolion Cosmetics Co., Ltd.
Category: otc | Type: HUMAN OTC DRUG LABEL
Date: 20200610

ACTIVE INGREDIENTS: Alcohol 0.7 kg/1 L
INACTIVE INGREDIENTS: Water; CARBOMER HOMOPOLYMER, UNSPECIFIED TYPE; TROLAMINE; Glycerin; Propylene Glycol; Panthenol; GLYCYRRHIZINATE DIPOTASSIUM; ALOE VERA LEAF; HYALURONATE SODIUM; .ALPHA.-TOCOPHEROL ACETATE

ACTIVE INGREDIENT

Alcohol 70.0% w/w

INACTIVE INGREDIENTS

Water, Carbomer, Triethanolamine, Glycerin, Propylene Glycol, Panthenol, Dipotassium Glycyrrhizate, Aloe Barbadensis Leaf Juice, Sodium Hyaluronate, Tocopheryl Acetate, Rosemary Extract

PURPOSE

SANITIZER

WARNINGS

For external use only. Flammable. Keep away from heat or flame

--------------------------------------------------------------------------------------------------------
Do not use
• in children less than 2 months of age
• on open skin wounds
--------------------------------------------------------------------------------------------------------
When using this product keep out of eyes, ears, and mouth. In case of contact with eyes, rinse eyes thoroughly with water.
--------------------------------------------------------------------------------------------------------
Stop use and ask a doctor if irritation or rash occurs. These may be signs of a serious condition.

KEEP OUT OF REACH OF CHILDREN

If swallowed, get medical help or contact a Poison Control Center right away.

Uses

Hand sanitizer to help reduce bacteria on the skin that could cause disease.

Recommended for repeated use.

Directions

Take an appropriate amount on your hands and rub thoroughly to dry.

Children under 6 years of age should be supervised when using this product.

Other Information

• Store between 15-30℃ (59-86℉)

• Avoid freezing and excessive heat above 40℃ (104℉)